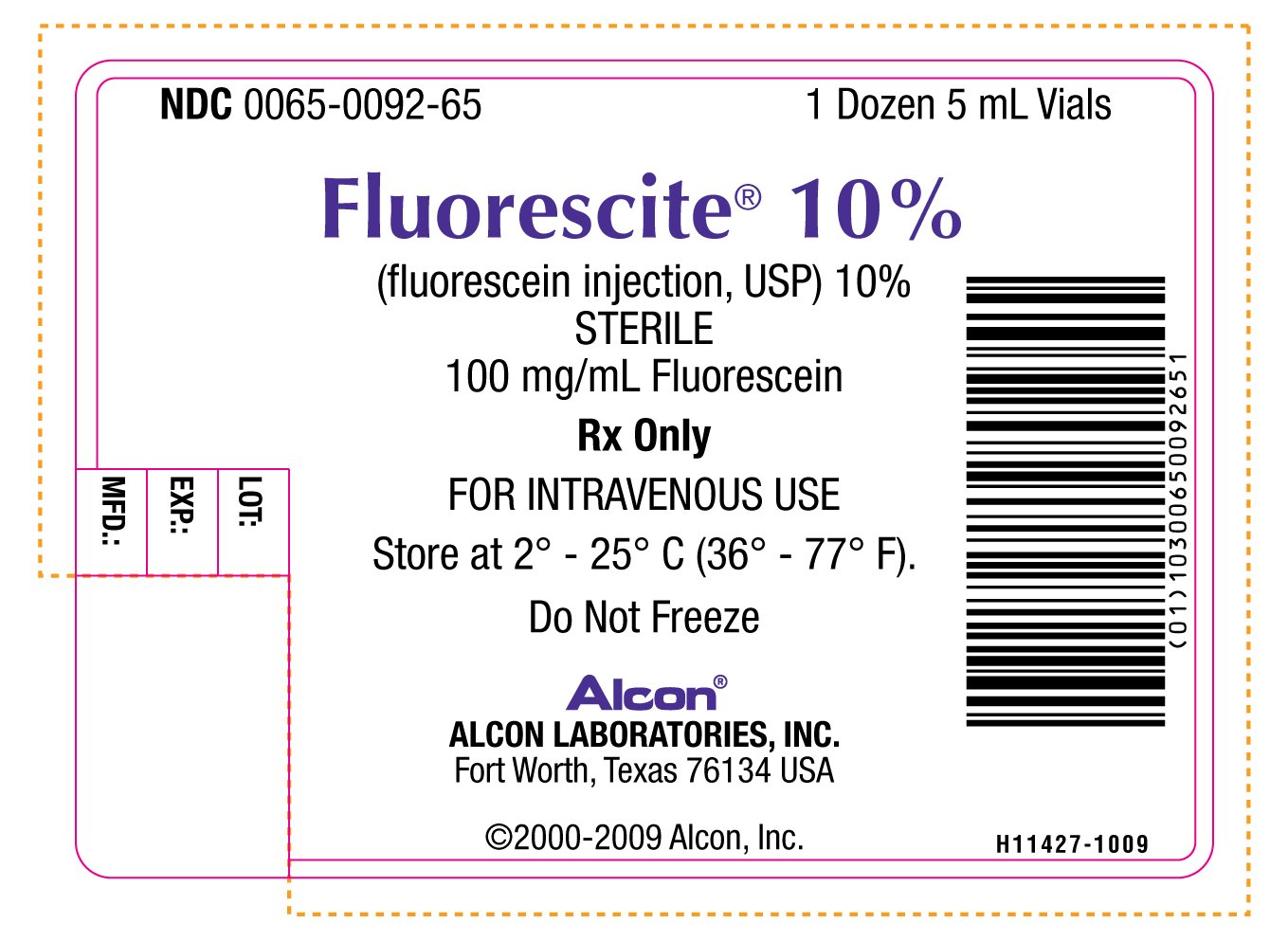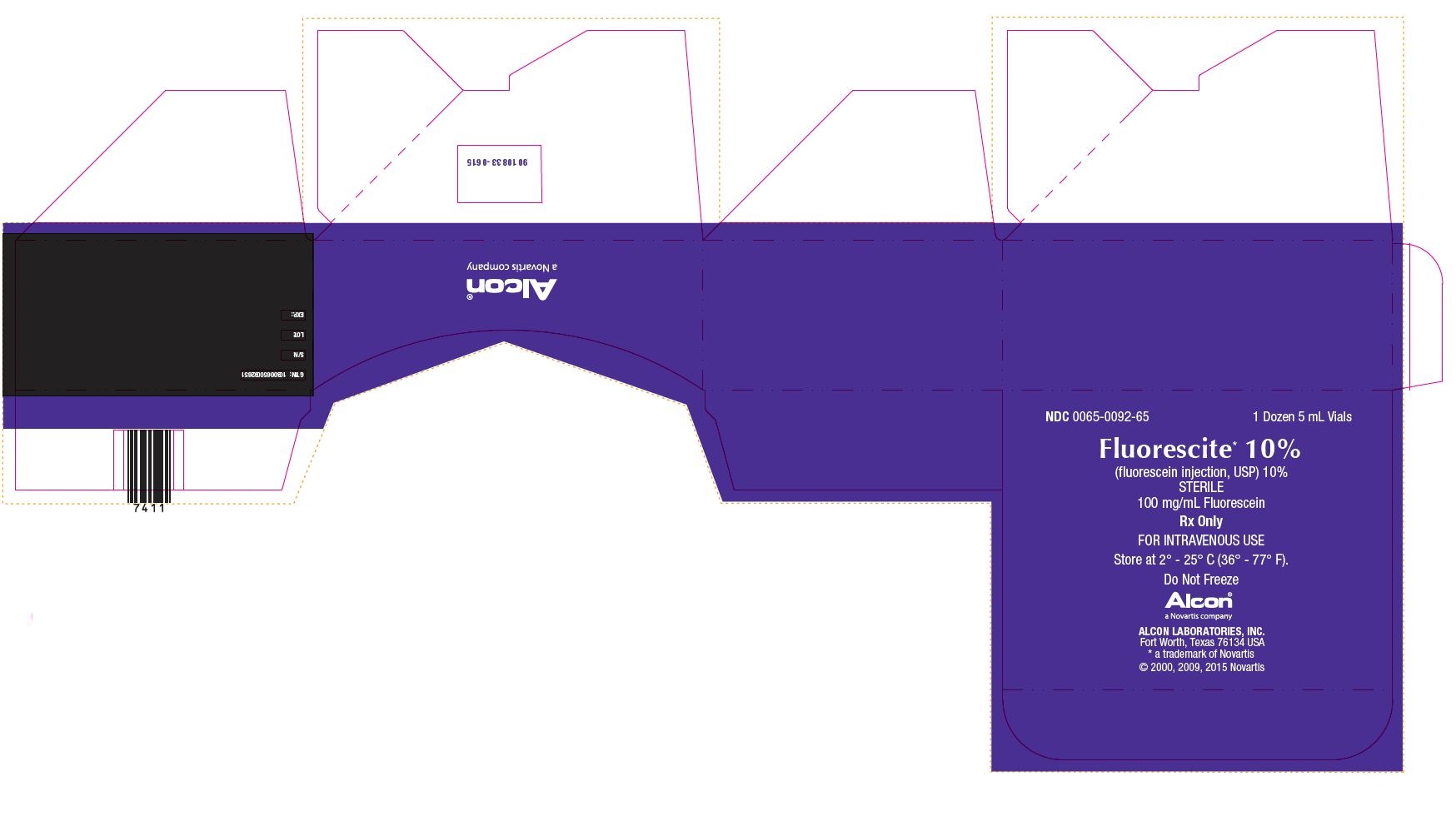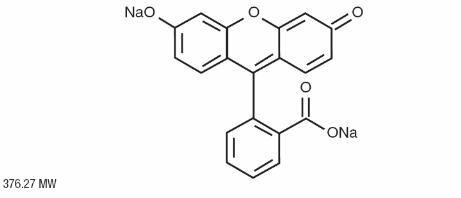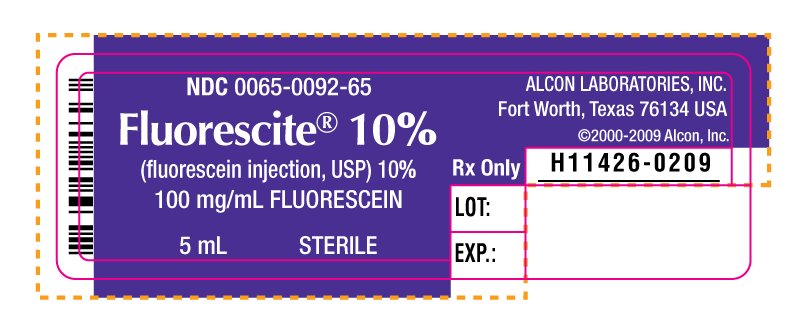 DRUG LABEL: FLUORESCITE
NDC: 0065-0092 | Form: INJECTION, SOLUTION
Manufacturer: Alcon, Inc.
Category: prescription | Type: HUMAN PRESCRIPTION DRUG LABEL
Date: 20231214

ACTIVE INGREDIENTS: FLUORESCEIN SODIUM 100 mg/1 mL
INACTIVE INGREDIENTS: SODIUM HYDROXIDE; HYDROCHLORIC ACID; WATER

HIGHLIGHTS OF PRESCRIBING INFORMATION

These highlights do not include all the information needed to use FLUORESCITE® safely and effectively.
See full prescribing information for FLUORESCITE® (fluorescein injection, USP) 10%.
FLUORESCITE® (fluorescein injection, USP) 10% Intravenous injection
Initial U.S. Approval: 1976

1 INDICATIONS AND USAGE

FLUORESCITE® Injection 10% is indicated in diagnostic fluorescein angiography or angioscopy of the retina and iris vasculature. (1)

2 DOSAGE AND ADMINISTRATION

The normal adult dose of FLUORESCITE® Injection 10% (100 mg/mL) is 500 mg via intravenous administration. (2.1)

For children, the dose should be calculated on the basis of 7.7 mg for each kg of actual body weight (or 35 mg for each 10 pounds of body weight) up to a maximum of 500 mg via intravenous administration. (2.1)

3 DOSAGE FORMS AND STRENGTHS

Single use 5 mL vial containing 100 mg/mL fluorescein. (3)

4 CONTRAINDICATIONS

FLUORESCITE® Injection 10% is contraindicated in patients with known hypersensitivity to fluorescein sodium or any other ingredients in this product (4.1)

5 WARNINGS AND PRECAUTIONS

Respiratory reactions may require intervention. (5.1)
Severe local tissue damage can occur with extravasation during injection. (5.2)
Nausea and/or vomiting may occur within minutes following injection. (5.3)

6 ADVERSE REACTIONS

The most common adverse reactions include skin discoloration, urine discoloration, nausea, vomiting, and gastrointestinal distress. (6)

To report SUSPECTED ADVERSE REACTIONS, contact Alcon Laboratories,Inc. at 1-800-757-9195 or FDA at 1-800-FDA-1088 or www.fda.gov/medwatch.

8 USE IN SPECIFIC POPULATIONS

Caution should be exercised when fluorescein sodium is administered to a nursing woman. (8.3)

FULL PRESCRIBING INFORMATION

1 INDICATIONS AND USAGE

FLUORESCITE® Injection 10% is indicated in diagnostic fluorescein angiography or angioscopy of the retina and iris vasculature.

2 DOSAGE AND ADMINISTRATION

2.1 Dosing

Adult Dose- The normal adult dose of FLUORESCITE® Injection 10% (100 mg/mL) is 500 mg via intravenous administration.

For children, the dose should be calculated on the basis of 7.7 mg for each kg of actual body weight (or 35 mg for each 10 pounds of body weight) up to a maximum of 500 mg via intravenous administration.

2.2 Preparation for Administration

Parenteral drug products should be inspected visually for particulate matter and discoloration prior to administration. Do not mix or dilute with other solutions or drugs. Flush intravenous cannulas before and after drugs are injected to avoid physical incompatibility reactions.

2.3 Administration

Inject the dose rapidly (1 mL per second is normally recommended) intravenously into the antecubital vein, after taking precautions to avoid extravasation. A syringe, filled with FLUORESCITE®, may be attached to transparent tubing and a 23 gauge butterfly needle for injection. Insert the needle and draw the patient’s blood to the hub of the syringe so that a small air bubble separates the patient’s blood in the tubing from the fluorescein. With the room lights on, slowly inject the blood back into the vein while watching the skin over the needle tip. If the needle has extravasated, the patient’s blood will be seen to bulge the skin and the injection should be stopped before any fluorescein is injected. When assured that extravasation has not occurred, the room light may be turned off and the fluorescein injection completed. Luminescence usually appears in the retina and choroidal vessels in 7 to 14 seconds and can be observed by standard viewing equipment.

Reduction in dose from 5 mL to 2 mL of FLUORESCITE® Injection 10% may be appropriate in cases when a highly sensitive imaging system e.g., scanning laser ophthalmoscope is used.

3 DOSAGE FORMS AND STRENGTHS

Single use 5 mL vial containing 100 mg/mL fluorescein.

4 CONTRAINDICATIONS

FLUORESCITE® Injection 10% is contraindicated in patients with known hypersensitivity to fluorescein sodium or any other ingredients in this product. Rare cases of death due to anaphylaxis have been reported. [see Warnings and Precautions (5.1) and Adverse Reactions (6)].

Fluorescein sodium can induce serious intolerance reactions. These reactions of intolerance are always unpredictable but they are more frequent in patients who have previously experienced an adverse reaction after fluorescein injection (symptoms other than nausea and vomiting) or in patients with history of allergy such as food or drug induced urticaria, asthma, eczema, allergic rhinitis.

Detailed questioning of each patient is recommended before the angiography to evaluate any prior history of allergy.

5 WARNINGS AND PRECAUTIONS

5.1 Respiratory Reactions

Caution is to be exercised in patients with a history of allergy or bronchial asthma. An emergency tray should be available in the event of possible reaction to FLUORESCITE® Injection 10%.

If a potential allergy is suspected, an intradermal skin test may be performed prior to intravenous administration, i.e., 0.05 mL injected intradermally to be evaluated 30 to 60 minutes following injection. Given the sensitivity and specificity of skin testing, a negative skin test is not proof that a patient is not allergic to fluorescein.

5.2 Severe Local Tissue Damage

Care must be taken to avoid extravasation during injection as the high pH of fluorescein solution can result in severe local tissue damage. The following complications resulting from extravasation of fluorescein have been noted to occur: severe pain in the arm for several hours, sloughing of the skin, superficial phlebitis, subcutaneous granuloma, and toxic neuritis along the median curve in the antecubital area. When significant extravasation occurs, the injection should be discontinued and conservative measures to treat damaged tissue and to relieve pain should be implemented. [see Administration (2.3) and Adverse Reactions(6)].

5.3 Nausea and/or Vomiting

Nausea and/or vomiting and gastrointestinal distress occur commonly within the first few minutes following injection. These reactions usually subside within 10 minutes.

6 ADVERSE REACTIONS

Skin and Urine Discoloration
The most common reaction is temporary yellowish discoloration of the skin and urine. Urine may attain a bright yellow color. Discoloration of the skin usually fades in 6 to 12 hours and usually fades in urine in 24 to 36 hours.

Gastrointestinal Reactions
Nausea, vomiting, and gastrointestinal distress are common adverse events. A strong taste may develop after injection.

Hypersensitivity Reactions
Symptoms and signs of hypersensitivity have occurred. Generalized hives and itching, bronchospasm and anaphylaxis have been reported. Rare cases of death have been reported. [see Contraindications (4.1) and Warnings and Precautions (5.1)].

Cardiopulmonary Reactions
Cardiac arrest, basilar artery ischemia, severe shock and death may occur rarely.

Neurologic Reactions
Headache may occur. Convulsions and syncope may rarely occur following injection.

Thrombophlebitis
Thrombophlebitis at the injection site has been reported. Extravasation of the solution at the injection site causes intense pain at the site and a dull aching pain in the injected arm. [see Administration (2.3) and Warnings and Precautions (5.2)].

8 USE IN SPECIFIC POPULATIONS

8.1 Pregnancy

Adequate animal reproduction studies have not been conducted with fluorescein sodium. It is also not known whether fluorescein sodium can cause fetal harm when administered to a pregnant woman. Fluorescein sodium should be given to a pregnant woman only if clearly needed.

8.3 Nursing Mothers

Fluorescein sodium injection has been demonstrated to be excreted in human milk for up to 4 days. Following fluorescein angiography, breast-feeding should therefore be discontinued for at least 4 days and the milk should be pumped off and discarded during this period.

8.4 Pediatric Use

Pediatric patients have been included in clinical studies. No overall differences in safety or effectiveness have been observed between pediatric and adult patients.

8.5 Geriatric Use

No overall differences in safety or effectiveness have been observed between elderly and other adult patients.

11 DESCRIPTION

FLUORESCITE® (fluorescein injection, USP) 10% contains fluorescein sodium (equivalent to fluorescein 10% w/v). It is a sterile solution for use intravenously as a diagnostic aid. Its chemical name is spiro[isobenzofuran-1(3H),9'-[9H]xanthene]-3-one, 3'6'-dihydroxy, disodium salt. The active ingredient is represented by the chemical structure:

FLUORESCITE® (fluorescein injection, USP) 10% is supplied as a sterile, unpreserved, unit dose aqueous solution, that has a pH of 8.0 – 9.8 and an osmolality of 572-858 mOsm/kg.

Active ingredient: fluorescein sodium

Inactive Ingredients: Sodium hydroxide and/or hydrochloric acid (to adjust pH), and water for injection.

12 CLINICAL PHARMACOLOGY

12.1 Mechanism of Action

Fluorescein sodium responds to electromagnetic radiation and light between the wavelengths of 465-490 nm and fluoresces, i.e., emits light at wavelengths of 520-530 nm. Thus, the hydrocarbon is excited by blue light and emits light that appears yellowish-green. Following intravenous injection of fluorescein sodium in an aqueous solution, the unbound fraction of the fluorescein can be excited with a blue light flash from a fundus camera as it circulates through the ocular vasculature, and the yellowish green fluorescence of the dye is captured by the camera. In the fundus, the fluorescence of the dye demarcates the retinal and/or choroidal vasculature under observation, distinguishing it from adjacent areas/structures.

12.3 Pharmacokinetics

Distribution:

Within 7 to 14 seconds after intravenous (IV) administration into antecubital vein, fluorescein usually appears in the central artery of the eye. Within a few minutes of IV administration of fluorescein sodium, a yellowish discoloration of the skin occurs, which begins to fade after 6 to 12 hours of dosing. Various estimates of volume of distribution indicate that fluorescein distributes well into interstitial space (0.5 L/kg).

Metabolism:

Fluorescein undergoes rapid metabolism to fluorescein monoglucuronide. After IV administration of fluorescein sodium (14 mg/kg) to 7 healthy subjects, approximately 80% of fluorescein in plasma was converted to glucuronide conjugate after a period of 1 hour post dose, indicating relatively rapid conjugation.

Excretion:

Fluorescein and its metabolites are mainly eliminated via renal excretion. After IV administration, the urine remains slightly fluorescent for 24 to 36 hours. A renal clearance of 1.75 mL/min/kg and a hepatic clearance (due to conjugation) of 1.50 mL/min/kg have been estimated. The systemic clearance of fluorescein was essentially complete by 48 to 72 hours after administration of 500 mg fluorescein.

13 NONCLINICAL TOXICOLOGY

13.1 Carcinogenesis, Mutagenesis, Impairment of Fertility

There have been no long-term studies done using fluorescein in animals to evaluate carcinogenic potential.

16 HOW SUPPLIED/STORAGE AND HANDLING

16.1 How Supplied

FLUORESCITE®(fluorescein injection, USP) 10% is supplied in a single use 5 mL glass vial with a gray FluroTec coated chlorobutyl stopper and purple flip-off aluminum seal. The vial stopper is not made with natural rubber latex. The vial contains a sterile, red-orange solution of fluorescein sodium.

NDC 0065-0092-65

16.2 Storage

Store at 2°- 25°C (36°- 77°F).
Do Not Freeze

17 PATIENT COUNSELING INFORMATION

After administration of fluorescein sodium, skin will attain a temporary yellowish discoloration. Urine attains a bright yellow color. Discoloration of the skin usually fades in 6 to 12 hours and usually fades in urine in 24 to 36 hours. [see Adverse Reactions (6)]

Distributed By:
ALCON LABORATORIES, INC.
Fort Worth, Texas 76134 USA
© 2006, 2016 Novartis
Revised: 2/2016
9014068-0117

PRINCIPAL DISPLAY PANEL

NDC 0065-0092-65 1 Dozen 5 mL Vials
Florescite® 10%
(fluorescein injection, USP) 10%
STERILE
100 mg/mL Fluorescein
Rx Only
FOR INTRAVENOUS USE
Store at 2° - 25° C (36° - 77° F)
Do Not Freeze
Alcon®
ALCON LABORATORIES, INC.
Fort Worth, Texas 76134 USA
©2000-2009 Alcon, Inc.
H11427-1009
LOT:
EXP.:
MFD.:

NDC 0065-0092-65 1 Dozen 5 mL Vials
Florescite* 10%
(fluorescein injection, USP) 10%
STERILE
100 mg/mL Fluorescein
Rx Only
FOR INTRAVENOUS USE
Store at 2° - 25° C (36° - 77° F)
Do Not Freeze
Alcon®
a Novartis company
Alcon Laboratories, Inc.
Fort Worth, Texas 76134 USA
* a trademark of Norvatis
©2000, 2009, 2015 Novartis
GTIN: 10300650092651
S/N:
LOT:
EXP.:
9010833-0615

NDC 0065-0092-65
Fluorescite® 10%
(fluorescein injection, USP) 10%
100 mg/mL FLUORESCEIN
5 mL STERILE
ALCON LABORATORIES, INC.
Fort Worth, Texas 76134 USA
©2000-2009 Alcon, Inc.
Rx Only
H11426-0209
LOT:
EXP.: